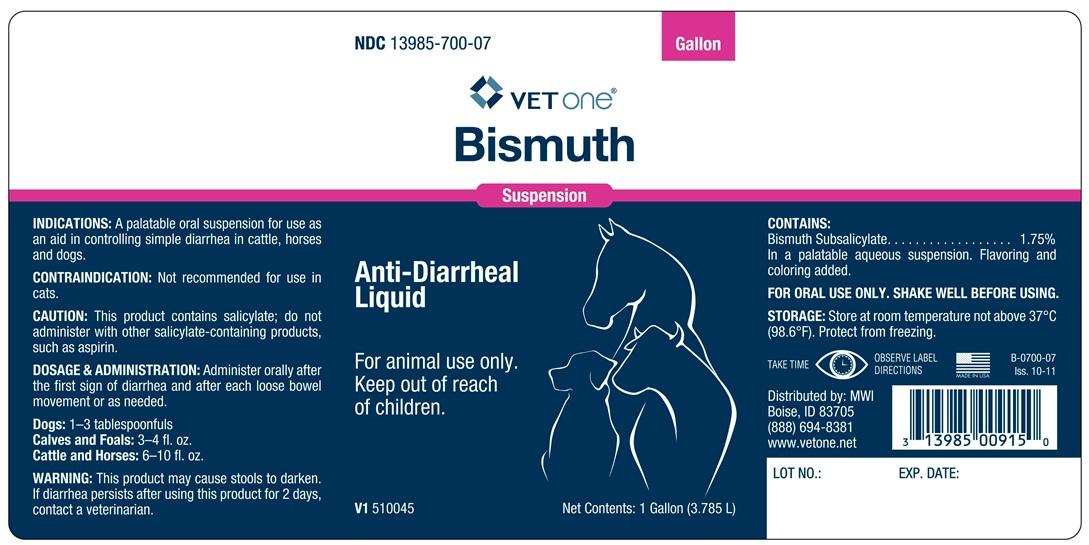 DRUG LABEL: BISMUTH
NDC: 13985-700 | Form: SUSPENSION
Manufacturer: MWI Veterinary Supply, Inc.
Category: animal | Type: OTC ANIMAL DRUG LABEL
Date: 20180117

ACTIVE INGREDIENTS: BISMUTH SUBSALICYLATE 66.2 mg/3.785 L

BISMUTH SUSPENSION

INDICATIONS AND USAGE

Anti-Diarrheal Liquid

For animal use only.

Keep out of reach of children

FOR ORAL USE ONLY.

SHAKE WELL BEFORE USING.

INDICATIONS:

A palatable oral suspension for use as an aid in controlling simple diarrhea in cattle, horses and dogs.

CONTRAINDICATIONS

Not recommended for use in cats.

CAUTION

This product contains salicylate; do not adminster with other salicylate-containing products, such as aspirin.

DOSAGE AND ADMINISTRATION

Administer orally after the first sign of diarrhea and after each loose bowel movement or as needed.

Dogs: 1 to 3 tablespoonfuls
Calves and Foals: 3 to 4 ounces
Cattle and Horses-- 6-10 fl. ozs.

WARNING

This product may cause stools to darken. If diarhea persists after using this product for 2 days, contact a veterinarian.

COMPOSITION

Bismuth Subsalicylate .................. 1.75%
in a palatable aqueous suspension. Flavoring and coloring added.

STORAGE

Store at room temperature not above 37oC (98.6oF). Protect from freezing.
TAKE TIME OBSERVE LABEL DIRECTIONS